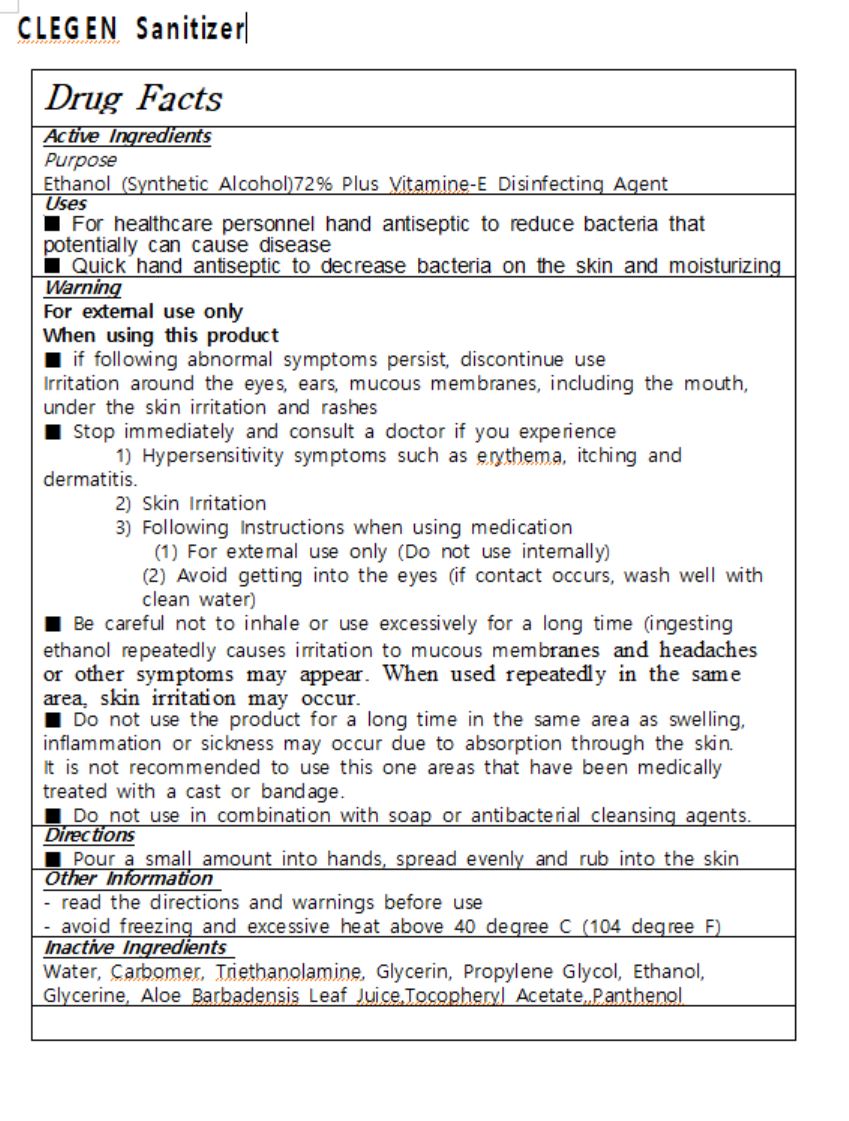 DRUG LABEL: CLEGEN Sanitizer
NDC: 74715-0001 | Form: GEL
Manufacturer: KB Global
Category: otc | Type: HUMAN OTC DRUG LABEL
Date: 20200409

ACTIVE INGREDIENTS: ALCOHOL 72 g/100 mL
INACTIVE INGREDIENTS: ALOE VERA LEAF; PROPYLENE GLYCOL; GLYCERIN; CARBOMER 940; .ALPHA.-TOCOPHEROL ACETATE; TROLAMINE; WATER

Drug Facts

ACTIVE INGREDIENT

alcohol

INACTIVE INGREDIENT

Water, Carbomer, Triethanolamine, Glycerin, Propylene Glycol, Glycerine, Aloe Barbadensis Leaf Juice,Tocopheryl Acetate,,Panthenol

PURPOSE

Disinfecting Agent

KEEP OUT OF REACH OF THE CHILDREN

INDICATIONS AND USAGE

Apply to clean, dry hands. Apply sufficient amount to thoroughly wet all surfaces of hands and fingers. Rub onto hands until dry.

Supervise children in the use of this product.

WARNINGS

■ Flammable. Keep away from fire or flame.

■ For external use only.

■ Do not use in eyes.

■ lf swallowed, get medical help promptly.

■ Stop use, ask doctor lf irritation occurs.

■ Keep out of reach of children.

DOSAGE AND ADMINISTRATION

for external use only